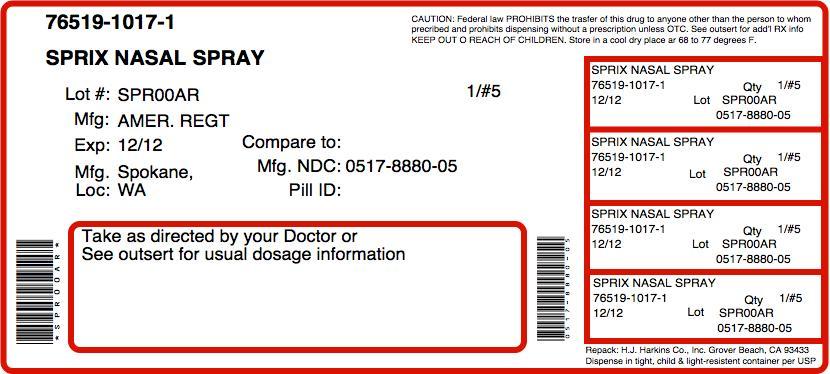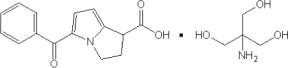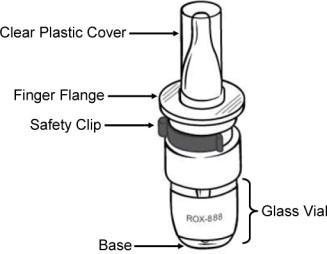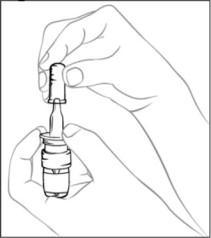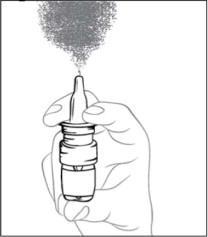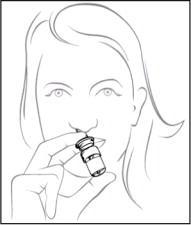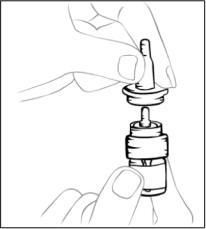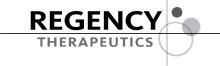 DRUG LABEL: Sprix
NDC: 76519-1017 | Form: SPRAY, METERED
Manufacturer: H.J. Harkins Company, Inc.
Category: prescription | Type: HUMAN PRESCRIPTION DRUG LABEL
Date: 20121029

ACTIVE INGREDIENTS: ketorolac tromethamine 15.75 mg/1 1
INACTIVE INGREDIENTS: edetate disodium; POTASSIUM PHOSPHATE, MONOBASIC; sodium hydroxide; water

HIGHLIGHTS OF PRESCRIBING INFORMATION

These highlights do not include all the information needed to use SPRIX® safely and effectively. See full prescribing information for SPRIX.
SPRIX® (ketorolac tromethamine) Nasal Spray
Initial U.S. Approval: 1989

WARNING; LIMITATIONS OF USE, GASTROINTESTINAL, BLEEDING, CARDIOVASCULAR, and RENAL RISK

See full prescribing information for complete boxed warning.

- Limitations of Use – The total duration of use of SPRIX and other ketorolac formulations should not exceed 5 days. (2.1)
- Gastrointestinal (GI) Risk – Ketorolac can cause peptic ulcers, GI bleeding, and/or perforation of the stomach or intestines, which can be fatal. SPRIX is CONTRAINDICATED in patients with peptic ulcer disease or history of GI bleeding. (4)
- Bleeding Risk – SPRIX inhibits platelet function and is CONTRAINDICATED in patients with suspected or confirmed cerebrovascular bleeding, hemorrhagic diathesis, incomplete hemostasis, or high risk of bleeding. (4)
- Cardiovascular (CV) Risk – NSAIDs may cause an increased risk of serious CV thrombotic events, myocardial infarction, and stroke, which can be fatal. This risk may increase with duration of use. Patients with CV disease or risk factors for CV disease may be at greater risk. (5.6) SPRIX is CONTRAINDICATED for treatment of peri-operative pain in the setting of coronary artery bypass graft (CABG) surgery. (4)
- Renal risk – SPRIX is CONTRAINDICATED in patients with advanced renal impairment and in patients at risk for renal failure due to volume depletion. (4)

1 INDICATIONS AND USAGE

SPRIX is indicated in adult patients for the short term (up to 5 days) management of moderate to moderately severe pain that requires analgesia at the opioid level. (1)

2 DOSAGE AND ADMINISTRATION

- For adult patients < 65 years of age: 31.5 mg (one 15.75 mg spray in each nostril) every 6 to 8 hours. The maximum daily dose is 126 mg. (2.2)
- For patients ≥ 65 years of age, renally impaired patients, and patients less than 50 kg (110 lbs): 15.75 mg (one 15.75 mg spray in only one nostril) every 6 to 8 hours. The maximum daily dose is 63 mg. (2.3)
- SPRIX has not been shown to be safe and effective in pediatric patients. (2.1)
- SPRIX nasal spray should be discarded within 24 hours of taking the first dose, even if the bottle still contains some medication. (2.4)

3 DOSAGE FORMS AND STRENGTHS

Nasal spray: 15.75 mg of ketorolac tromethamine in each 100 μL spray. Each 1.7 g bottle contains 8 sprays. (3)

4 CONTRAINDICATIONS

- Known hypersensitivity to ketorolac, aspirin, other NSAIDs, or EDTA (4, 5.5, 5.7, 5.11)
- Use in patients with active peptic ulcer disease, recent GI bleeding or perforation, or a history of peptic ulcers or GI bleeding (4, 5.2)
- Use in patients with a history of asthma, urticaria, or other allergic-type reactions after taking aspirin or other NSAIDs (4, 5.5, 5.7, 5.11)
- Use as a prophylactic analgesic before any major surgery (4, 5.3)
- Use during the perioperative period in the setting of coronary artery bypass graft (CABG) surgery (4, 5.6)
- Use in patients with advanced renal disease or patients at risk for renal failure due to volume depletion (4, 5.4, 5.6)
- Use in labor and delivery (4, 5.8)
- Use in patients with suspected or confirmed cerebrovascular bleeding, patients with hemorrhagic diathesis, incomplete hemostasis, and those at high risk of bleeding (4, 5.3)

5 WARNINGS AND PRECAUTIONS

- SPRIX should not be used concomitantly with IM/IV or oral ketorolac, aspirin, or other NSAIDs. (5.1)
- Ketorolac can cause serious GI adverse events including bleeding, ulceration, and perforation. SPRIX should be prescribed with caution in patients with a prior history of ulcer disease or GI bleeding. Elderly patients are at greater risk for serious GI events. (4, 5.2)
- NSAIDs affect platelet aggregation and may cause bleeding complications. SPRIX should be used with caution in patients who have coagulation disorders or are on therapy that affects hemostasis. Do not use SPRIX in patients for whom hemostasis is critical. (4, 5.3)
- Ketorolac can cause renal injury. SPRIX should not be used in patients with advanced renal disease or patients at risk for renal failure due to volume depletion, and should be used with caution in patients taking diuretics or ACE inhibitors. (4, 5.4, 12.4)
- Anaphylactoid reactions may occur in patients with or without a history of allergic reactions to aspirin or NSAIDs. SPRIX should be discontinued immediately in patients with allergic reactions. (4, 5.5, 5.7, 5.11)
- Serious and potentially fatal cardiovascular thrombotic events, myocardial infarction, and stroke can occur with NSAID treatment. (5.6)
- Fluid retention and edema have been observed in patients taking NSAIDs. SPRIX should be used with caution in patients with cardiac decompensation or similar conditions. (5.4, 5.6)
- NSAIDs can cause serious dermatologic adverse reactions such as exfoliative dermatitis, Stevens-Johnson syndrome, and toxic epidermal necrolysis, which can be fatal. SPRIX should be discontinued immediately in patients with skin reactions. (4, 5.7)
- During pregnancy, use of SPRIX beyond 30 weeks gestation can cause premature closure of the ductus arteriosus, resulting in fetal harm. (5.8)

6 ADVERSE REACTIONS

The most common adverse reactions (incidence > 2%) in patients treated with SPRIX and occurring at a rate at least twice that of placebo are nasal discomfort, rhinalgia, increased lacrimation, throat irritation, oliguria, rash, bradycardia, decreased urine output, increased ALT and/or AST, hypertension, and rhinitis. (6.1)

To report SUSPECTED ADVERSE REACTIONS, contact American Regent, Inc. at 1-800-734-9236 or FDA at 1-800-FDA-1088 or www.fda.gov/medwatch

7 DRUG INTERACTIONS

- Concomitant use with anticoagulants may increase the risk of serious GI bleeding. (7.1)

FULL PRESCRIBING INFORMATION

WARNING; LIMITATIONS OF USE, GASTROINTESTINAL, BLEEDING, CARDIOVASCULAR, and RENAL RISK

Limitations of Use

SPRIX (ketorolac tromethamine), a nonsteroidal anti-inflammatory drug (NSAID), is indicated for short-term (up to 5 days in adults) management of moderate to moderately severe pain that requires analgesia at the opioid level. Do not exceed a total combined duration of use of SPRIX and other ketorolac formulations (IM/IV or oral) of 5 days [see Dosage and Administration, (2.1) and Warnings and Precautions (5.1)].

SPRIX is not indicated for use in pediatric patients and it is not indicated for minor or chronic painful conditions.

Gastrointestinal Risk

Ketorolac tromethamine, including SPRIX, can cause peptic ulcers, gastrointestinal bleeding and/or perforation of the stomach or intestines, which can be fatal. These events can occur at any time during use and without warning symptoms. Therefore, SPRIX is contraindicated in patients with active peptic ulcer disease, in patients with recent gastrointestinal bleeding or perforation, and in patients with a history of peptic ulcer disease or gastrointestinal bleeding. Elderly patients are at greater risk for serious gastrointestinal events [see Contraindications (4), Warnings and Precautions (5.2)].

Bleeding Risk

Ketorolac tromethamine inhibits platelet function and is, therefore, contraindicated in patients with suspected or confirmed cerebrovascular bleeding, patients with hemorrhagic diathesis, incomplete hemostasis and those at high risk of bleeding [see Contraindications (4), Warnings and Precautions (5.3)].

Cardiovascular Risk

NSAIDs may cause an increased risk of serious cardiovascular thrombotic events, myocardial infarction, and stroke, which can be fatal. This risk may increase with duration of use. Patients with cardiovascular disease or risk factors for cardiovascular disease may be at greater risk [see Warnings and Precautions (5.6)].

SPRIX Nasal spray is contraindicated for treatment of peri-operative pain in the setting of coronary artery bypass graft (CABG) surgery [see Contraindications (4)].

Renal Risk

SPRIX is contraindicated in patients with advanced renal impairment and in patients at risk for renal failure due to volume depletion [see Contraindications (4), Warnings and Precautions (5.4)].

1 INDICATIONS AND USAGE

SPRIX is indicated in adult patients for the short term (up to 5 days) management of moderate to moderately severe pain that requires analgesia at the opioid level.

2 DOSAGE AND ADMINISTRATION

2.1 Limitations of Use

The total duration of use of SPRIX alone or sequentially with other formulations of ketorolac (IM/IV or oral) must not exceed 5 days because of the potential for increasing the frequency and severity of adverse reactions associated with the recommended doses [see Warnings and Precautions (5.1)]. Treat patients for the shortest duration possible, and do not exceed 5 days of therapy with SPRIX.

Do not use SPRIX concomitantly with other formulations of ketorolac or other NSAIDs [see Warnings and Precautions (5.1)].

SPRIX has not been shown to be safe and effective in pediatric patients 17 years of age and younger.

2.2 Adult Patients < 65 Years of Age

The recommended dose is 31.5 mg SPRIX (one 15.75 mg spray in each nostril) every 6 to 8 hours. The maximum daily dose is 126 mg (four doses).

2.3 Reduced Doses for Special Populations

For patients ≥ 65 years of age, renally impaired patients, and adult patients less than 50 kg (110 lbs), the recommended dose is 15.75 mg SPRIX (one 15.75 mg spray in only one nostril) every 6 to 8 hours. The maximum daily dose is 63 mg (four doses) [see Warnings and Precautions (5.2, 5.4)].

2.4 Discard Used SPRIX Bottle after 24 Hours

Do not use any single SPRIX bottle for more than one day as it will not deliver the intended dose after 24 hours. Therefore, the bottle must be discarded no more than 24 hours after taking the first dose, even if the bottle still contains some liquid.

3 DOSAGE FORMS AND STRENGTHS

Nasal spray: 15.75 mg of ketorolac tromethamine in each 100 μL spray. Each 1.7 g bottle contains 8 sprays.

4 CONTRAINDICATIONS

- Known hypersensitivity to ketorolac tromethamine [see Warnings and Precautions (5.5, 5.7, 5.11)]
- Use in patients with active peptic ulcer disease, in patients with recent gastrointestinal bleeding or perforation, and in patients with a history of peptic ulcer disease or gastrointestinal bleeding [see Warnings and Precautions (5.2)]
- Use in patients with a history of asthma, urticaria, or other allergic-type reactions after taking aspirin or other NSAIDs [see Warnings and Precautions (5.5, 5.7, 5.11)]
- Use as a prophylactic analgesic before any major surgery [see Warnings and Precautions (5.3)]
- Use during the perioperative period in the setting of coronary artery bypass graft (CABG) surgery [see Warnings and Precautions (5.6)]
- Use in patients with advanced renal disease or patients at risk for renal failure due to volume depletion [see Warnings and Precautions (5.4,5.6)]
- Use in labor and delivery. Through its prostaglandin synthesis inhibitory effect, ketorolac may adversely affect fetal circulation and inhibit uterine contractions, thus increasing the risk of uterine hemorrhage.[see Warnings and Precautions (5.8), Use in Specific Populations (8.1, 8.2)]
- Use in nursing mothers because of the potential adverse effects of prostaglandin-inhibiting drugs on neonates
- Use in patients with suspected or confirmed cerebrovascular bleeding, hemorrhagic diathesis, incomplete hemostasis, or those for whom hemostasis is critical [see Warnings and Precautions (5.3), Drug Interactions (7.1, 7.10)]
- Known hypersensitivity to aspirin or to other NSAIDs [see Warnings and Precautions (5.5, 5.7, 5.11)]
- Known hypersensitivity to ethylenediamine tetraacetic acid (EDTA) [see Description (11)]
- Concomitant use with probenecid [see Drug Interactions (7.4)]
- Concomitant use with pentoxifylline [see Drug Interactions (7.10)]

5 WARNINGS AND PRECAUTIONS

5.1 Limitations of Use

The total duration of use of SPRIX alone or sequentially with other forms of ketorolac is not to exceed 5 days. SPRIX must not be used concomitantly with other forms of ketorolac or other NSAIDs [see Dosage and Administration (2.1)].

5.2 Gastrointestinal (GI) Effects - Risk of Ulceration, Bleeding, and Perforation

SPRIX is contraindicated in patients with previously documented peptic ulcers and/or GI bleeding [see Contraindications (4)]. Ketorolac tromethamine can cause serious GI adverse events including bleeding, ulceration, and perforation of the stomach, small intestine, or large intestine, which can be fatal. These serious adverse events can occur at any time, with or without warning symptoms, in patients treated with ketorolac.

Only one in five patients who develop a serious upper GI adverse event on NSAID therapy is symptomatic. Minor upper GI problems, such as dyspepsia, are common and may also occur at any time during NSAID therapy. The incidence and severity of GI complications increases with increasing dose of, and duration of treatment with, ketorolac. Even short-term therapy is not without risk. In addition to past history of ulcer disease, other factors that increase the risk for GI bleeding in patients treated with NSAIDs include concomitant use of oral corticosteroids or anticoagulants, longer duration of NSAID therapy, smoking, use of alcohol, older age, and poor general health status. Most spontaneous reports of fatal GI events are in elderly or debilitated patients, and therefore, special care should be taken in treating this population.

To minimize the potential risk for an adverse GI event, the lowest effective dose should be used for the shortest possible duration. Remain alert for signs and symptoms of GI ulceration and bleeding during NSAID therapy, and promptly initiate additional evaluation and treatment if a serious GI adverse event is suspected. This should include discontinuation of SPRIX until a serious GI adverse event is ruled out. For high risk patients, consider alternate therapies that do not involve NSAIDs. Use great care when giving SPRIX to patients with a history of inflammatory bowel disease (ulcerative colitis, Crohn's disease) as their condition may be exacerbated.

5.3 Hematological Effects

Because prostaglandins play an important role in hemostasis and NSAIDs affect platelet aggregation as well, use caution with use of ketorolac tromethamine in patients who have coagulation disorders, and monitor these patients carefully. The effects of NSAIDs other than aspirin on platelet function are reversible. Patients on therapeutic doses of anticoagulants (e.g., heparin or dicumarol derivatives) have an increased risk of bleeding complications if given ketorolac tromethamine concurrently; therefore, administer such concomitant therapy only with extreme caution. The concurrent use of ketorolac tromethamine and therapy that affects hemostasis, including prophylactic low dose heparin (2500 to 5000 units q12h), warfarin and dextrans, has not been studied extensively, but may also be associated with an increased risk of bleeding. Until data from such studies are available, carefully weigh the benefits against the risks and use such concomitant therapy in these patients only with extreme caution. Monitor patients receiving therapy that affects hemostasis closely.

In clinical trials, serious adverse events related to bleeding were more common in patients treated with SPRIX than placebo. In clinical trials and in postmarketing experience with ketorolac IV and IM dosing, postoperative hematomas and other signs of wound bleeding have been reported in association with peri-operative use. Therefore, use SPRIX with caution in the postoperative setting when hemostasis is critical.

Anemia is sometimes seen in patients receiving NSAIDs. This may be due to fluid retention, occult or gross GI blood loss, or an incompletely described effect upon erythropoiesis. Do not use SPRIX in patients for whom hemostasis is critical [see Contraindications (4), Drug Interactions (7.1, 7.2, 7.10)].

5.4 Renal Effects

Ketorolac and its metabolites are eliminated primarily by the kidneys. Patients with reduced creatinine clearance will have diminished clearance of the drug [see Clinical Pharmacology (12.4)]. SPRIX is contraindicated in patients with advanced renal impairment [see Contraindications (4)].

In patients in whom renal prostaglandins have a compensatory role in the maintenance of renal perfusion, administration of an NSAID may cause a dose-dependent reduction in prostaglandin formation and renal blood flow, which may precipitate overt renal decompensation. Decreased intravascular volume such as when oral intake is poor increases the risks of renal toxicity with NSAIDs. Therefore, patients treated with SPRIX should be adequately hydrated. Discontinuation of NSAID therapy is usually followed by recovery to the pretreatment state.

Use SPRIX with caution in patients with impaired renal function, heart failure, liver dysfunction, those taking diuretics or ACE inhibitors, and the elderly. Assess the risks and benefits prior to giving SPRIX to these patients, and follow these patients closely during SPRIX therapy. Long-term administration of NSAIDs has resulted in renal papillary necrosis and other renal injury such as interstitial nephritis and nephrotic syndrome.

5.5 Anaphylactoid Reactions

As with other NSAIDs, anaphylactoid reactions may occur in patients with or without a history of allergic reactions to aspirin or NSAIDs and in patients without known prior exposure to ketorolac. SPRIX should be discontinued immediately in patients with allergic reactions. SPRIX should not be given to patients with the aspirin triad. This symptom complex typically occurs in asthmatic patients who experience rhinitis with or without nasal polyps, or who exhibit severe, potentially fatal bronchospasm after taking aspirin or other NSAIDs [see Contraindications (4), Warnings and Precautions (5.11)]. Emergency help should be sought in cases where an anaphylactoid reaction occurs.

5.6 Cardiovascular Effects

- Cardiovascular (CV) Thrombotic Events

Clinical trials of several COX-2 selective and nonselective NSAIDs of up to three years duration have shown an increased risk of serious CV thrombotic events, myocardial infarction and stroke, which can be fatal. All NSAIDs, both COX-2 selective and nonselective, may have a similar risk. Patients with known CV disease or risk factors for CV disease may be at greater risk. To minimize the potential risk for an adverse CV event in patients treated with an NSAID, the lowest effective dose should be used for the shortest duration possible. Physicians and patients should remain alert for the development of such events, even in the absence of previous CV symptoms. Patients should be informed about the signs and/or symptoms of serious CV events and the steps to take if they occur. There is no consistent evidence that concurrent use of aspirin mitigates the increased risk of serious CV thrombotic events associated with NSAID use. The concurrent use of aspirin and an NSAID increases the risk of serious GI events. Two large, controlled clinical trials of a COX-2 selective NSAID for the treatment of pain in the first 10-14 days following CABG surgery found an increased incidence of myocardial infarction and stroke [see Contraindications (4), Warnings and Precautions (5.2), Drug Interactions (7.2, 7.3, 7.7)].

- Hypertension

NSAIDs can lead to onset of new hypertension or worsening of preexisting hypertension, either of which may contribute to the increased incidence of CV events. Patients taking thiazides or loop diuretics may have impaired response to these therapies when taking NSAIDs [see Drug Interactions (7.3)].

- Congestive Heart Failure and Edema

Fluid retention, edema, retention of NaCl, oliguria, and elevations of serum urea nitrogen and creatinine have been reported in clinical trials with ketorolac. Therefore, only use SPRIX very cautiously in patients with cardiac decompensation or similar conditions.

5.7 Skin Reactions

NSAIDs, including ketorolac, can cause serious skin adverse events such as exfoliative dermatitis, Stevens-Johnson Syndrome (SJS), and toxic epidermal necrolysis (TEN), which can be fatal. These serious events may occur without warning. Inform patients about the signs and symptoms of serious skin manifestations, and discontinue use of the drug at the first appearance of skin rash or any other sign of hypersensitivity [see Contraindications (4)].

5.8 Pregnancy

Starting at 30 weeks gestation, SPRIX can cause fetal harm when administered to a pregnant woman due to an increased risk of premature closure of the ductus arteriosus. If SPRIX is used at or after 30 weeks gestation, the patient should be apprised of the potential hazard to a fetus [see Use in Specific Populations (8.1)].

5.9 Hepatic Effects

Use SPRIX with caution in patients with impaired hepatic function or a history of liver disease. Borderline elevations of one or more liver tests may occur in up to 15% of patients taking NSAIDs, including ketorolac. These laboratory abnormalities may progress, may remain unchanged, or may be transient with continuing therapy. Notable elevations of ALT or AST (approximately three or more times the upper limit of normal) have been reported in approximately 1% of patients in clinical trials with NSAIDs. In addition, rare cases of severe hepatic reactions, including jaundice, fulminant hepatitis, liver necrosis, and hepatic failure, some of them with fatal outcomes, have been reported [see Warnings and Precautions (5.4, 5.6),Clinical Pharmacology (12.4)].

Evaluate patients with symptoms and/or signs suggesting liver dysfunction, or in whom an abnormal liver test has occurred, for evidence of the development of a more severe hepatic reaction while on therapy with SPRIX. If clinical signs and symptoms consistent with liver disease develop, or if systemic manifestations occur (e.g., eosinophilia, rash, etc.), discontinue SPRIX.

5.10 Inflammation and Fever

The pharmacological activity of SPRIX in reducing inflammation and fever may diminish the utility of these diagnostic signs in detecting infections.

5.11 Preexisting Asthma

Patients with asthma may have aspirin-sensitive asthma. The use of aspirin in patients with aspirin-sensitive asthma has been associated with severe bronchospasm which can be fatal. Since cross reactivity, including bronchospasm, between aspirin and other NSAIDs has been reported in such aspirin-sensitive patients, do not administer SPRIX to patients with this form of aspirin sensitivity, and use with caution in patients with preexisting asthma [see Contraindications (4), Warnings and Precautions (5.5)].

5.12 Eye Exposure

Avoid contact of SPRIX with the eyes. If eye contact occurs, wash out the eye with water or saline, and consult a physician if irritation persists for more than an hour.

6 ADVERSE REACTIONS

The following serious adverse reactions are discussed elsewhere in the labeling:

- Gastrointestinal effects [see Boxed Warning and Warnings and Precautions (5.2)]
- Hemorrhage [see Boxed Warning and Warnings and Precautions (5.3)]
- Renal effects [see Boxed Warning and Warnings and Precautions (5.4)]
- Anaphylactoid reactions [see Warnings and Precautions (5.5)]
- Cardiovascular thrombotic events [see Boxed Warning and Warnings and Precautions (5.6)]
- Hypertension [see Warnings and Precautions (5.6)]
- Congestive heart failure and edema [see Warnings and Precautions (5.6)]
- Serious skin reactions [see Warnings and Precautions (5.7)]
- Hepatic effects [see Warnings and Precautions (5.9)]

The most frequently reported adverse reactions were related to local symptoms, i.e., nasal discomfort or irritation. These reactions were generally mild and transient in nature.

The most common drug-related adverse events leading to premature discontinuation were nasal discomfort or nasal pain (rhinalgia).

6.1 Experience from SPRIX Clinical Studies

Because clinical trials are conducted under widely varying conditions, adverse reaction rates observed in the clinical trials of a drug cannot be directly compared to rates in the clinical trials of another drug and may not reflect the rates observed in practice.

The data described below reflect exposure to SPRIX in patients enrolled in placebo-controlled efficacy studies of acute pain following major surgery. The studies enrolled 828 patients (183 men, 645 women) ranging from 18 years to over 75 years of age.

The patients in the postoperative pain studies had undergone major abdominal, orthopedic, gynecologic, or other surgery; 455 patients received SPRIX (31.5 mg) three or four times a day for up to 5 days, and 245 patients received placebo. Most patients were receiving concomitant opioids, primarily PCA morphine.

Table 1. Post-operative Patients with Adverse Reactions Observed at a rate of 2% or more and at least twice the incidence of the placebo group.
 | SPRIX (N=455) | Placebo (N= 245)
Nasal discomfort | 15% | 2%
Rhinalgia | 13% | <1%
Lacrimation increased | 5% | 0%
Throat irritation | 4% | <1%
Oliguria | 3% | 1%
Rash | 3% | <1%
Bradycardia | 2% | <1%
Urine output decreased | 2% | <1%
ALT and/or AST increased | 2% | 1%
Hypertension | 2% | 1%
Rhinitis | 2% | <1%

In controlled clinical trials in major surgery, primarily knee and hip replacements and abdominal hysterectomies, seven patients (N=455, 1.5%) treated with SPRIX experienced serious adverse events of bleeding (4 patients) or hematoma (3 patients) at the operative site versus one patient (N=245, 0.4%) treated with placebo (hematoma). Six of the seven patients treated with SPRIX underwent a surgical procedure and/or blood transfusion and the placebo patient subsequently required a blood transfusion.

6.2 Adverse Reactions Reported in Clinical Trials with Other Dosage Forms of Ketorolac or Other NSAIDs

Adverse reaction rates increase with higher doses of ketorolac. It is necessary to remain alert for the severe complications of treatment with ketorolac, such as GI ulceration, bleeding, and perforation, postoperative bleeding, acute renal failure, anaphylactic and anaphylactoid reactions, and liver failure. These complications can be serious in certain patients for whom ketorolac is indicated, especially when the drug is used inappropriately.

In patients taking ketorolac or other NSAIDs in clinical trials, the most frequently reported adverse experiences in approximately 1% to 10% of patients are:

Gastrointestinal (GI) experiences including:

abdominal pain | constipation/diarrhea | dyspepsia
flatulence | GI fullness | GI ulcers (gastric/duodenal)
gross bleeding/perforation | heartburn | nausea*
stomatitis | vomiting
Other experiences:
abnormal renal function | anemia | dizziness
drowsiness | edema | elevated liver enzymes
headache* | hypertension | increased bleeding time
injection site pain | pruritus | purpura
rash | tinnitus | sweating
*Incidence greater than 10%

Additional adverse experiences reported occasionally (<1% in patients taking ketorolac or other NSAIDs in clinical trials) include:

Body as a Whole: fever, infection, sepsis

Cardiovascular System: congestive heart failure, palpitation, pallor, tachycardia, syncope

Digestive System: anorexia, dry mouth, eructation, esophagitis, excessive thirst, gastritis, glossitis, hematemesis, hepatitis, increased appetite, jaundice, melena, rectal bleeding

Hemic and Lymphatic: ecchymosis, eosinophilia, epistaxis, leukopenia, thrombocytopenia

Metabolic and Nutritional: weight change

Nervous System: abnormal dreams, abnormal thinking, anxiety, asthenia, confusion, depression, euphoria, extrapyramidal symptoms, hallucinations, hyperkinesis, inability to concentrate, insomnia, nervousness, paresthesia, somnolence, stupor, tremors, vertigo, malaise

Respiratory: asthma, dyspnea, pulmonary edema, rhinitis

Special Senses: abnormal taste, abnormal vision, blurred vision, hearing loss

Urogenital: cystitis, dysuria, hematuria, increased urinary frequency, interstitial nephritis, oliguria/polyuria, proteinuria, renal failure, urinary retention

6.3 Adverse Reactions from Postmarketing Experience with Other Dosage Forms of Ketorolac or Other NSAIDs

Other observed reactions (reported from postmarketing experience in patients taking ketorolac or other NSAIDs) are:

Body as a Whole: angioedema, death, hypersensitivity reactions such as anaphylaxis, anaphylactoid reaction, laryngeal edema, tongue edema, myalgia

Cardiovascular: arrhythmia, bradycardia, chest pain, flushing, hypotension, myocardial infarction, vasculitis

Dermatologic: exfoliative dermatitis, erythema multiforme, Lyell's syndrome, bullous reactions including Stevens-Johnson syndrome and toxic epidermal necrolysis

Gastrointestinal: acute pancreatitis, liver failure, ulcerative stomatitis, exacerbation of inflammatory bowel disease (ulcerative colitis, Crohn's disease)

Hemic and Lymphatic: agranulocytosis, aplastic anemia, hemolytic anemia, lymphadenopathy, pancytopenia, postoperative wound hemorrhage (rarely requiring blood transfusion)

Metabolic and Nutritional: hyperglycemia, hyperkalemia, hyponatremia

Nervous System: aseptic meningitis, convulsions, coma, psychosis

Respiratory: bronchospasm, respiratory depression, pneumonia

Special Senses: conjunctivitis

Urogenital: flank pain with or without hematuria and/or azotemia, hemolytic uremic syndrome

7 DRUG INTERACTIONS

Ketorolac is highly bound to human plasma protein (mean 99.2%). There is no evidence in animal or human studies that ketorolac induces or inhibits hepatic enzymes capable of metabolizing itself or other drugs.

7.1 Warfarin, Digoxin, Salicylate, and Heparin

The in vitro binding of warfarin to plasma proteins is only slightly reduced by ketorolac (99.5% control vs. 99.3%) when ketorolac plasma concentrations reach 5 to 10 mcg/mL. Ketorolac does not alter digoxin protein binding. In vitro studies indicate that, at therapeutic concentrations of salicylate (300 mcg/mL), the binding of ketorolac was reduced from approximately 99.2% to 97.5%, representing a potential twofold increase in unbound ketorolac plasma levels. Therapeutic concentrations of digoxin, warfarin, ibuprofen, naproxen, piroxicam, acetaminophen, phenytoin, and tolbutamide did not alter ketorolac protein binding.

The effects of warfarin and NSAIDs, in general, on GI bleeding are synergistic, such that the users of both drugs together have a risk of serious GI bleeding higher than the users of either drug alone.

7.2 Aspirin

When ketorolac is administered with aspirin, its protein binding is reduced, although the clearance of free ketorolac is not altered. The clinical significance of this interaction is not known; however, as with other NSAIDs, concomitant administration of SPRIX and aspirin is not generally recommended because of the potential of increased adverse effects [see Warnings and Precautions (5.2, 5.5, 5.11)].

7.3 Diuretics

Clinical studies, as well as postmarketing observations, have shown that ketorolac can reduce the natriuretic effect of furosemide and thiazides in some patients. This response has been attributed to inhibition of renal prostaglandin synthesis. During concomitant therapy with SPRIX, observe the patient closely for signs of renal failure [see Warnings and Precautions (5.4, 5.6)], as well as to assure diuretic efficacy.

7.4 Probenecid

Concomitant administration of oral ketorolac and probenecid resulted in decreased clearance and volume of distribution of ketorolac and significant increases in ketorolac plasma levels (total AUC increased approximately threefold from 5.4 to 17.8 mcg/h/mL), and terminal half-life increased approximately twofold from 6.6 to 15.1 hours. Therefore, concomitant use of SPRIX and probenecid is contraindicated.

7.5 Lithium

NSAIDs have produced an elevation of plasma lithium levels and a reduction in renal lithium clearance. The mean minimum lithium concentration increased 15%, and the renal clearance was decreased by approximately 20%. These effects have been attributed to inhibition of renal prostaglandin synthesis by the NSAID. Thus, when SPRIX and lithium are administered concurrently, observe patients carefully for signs of lithium toxicity.

7.6 Methotrexate

NSAIDs have been reported to competitively inhibit methotrexate accumulation in rabbit kidney slices. This may indicate that they could enhance the toxicity of methotrexate. Use caution when SPRIX is administered concomitantly with methotrexate.

7.7 ACE Inhibitors/Angiotensin II Receptor Antagonists

Concomitant use of ACE inhibitors and/or angiotensin II receptor antagonists may increase the risk of renal impairment, particularly in volume-depleted patients. Reports suggest that NSAIDs may diminish the antihypertensive effect of ACE inhibitors and/or angiotensin II receptor antagonists. Consider this interaction in patients taking SPRIX concomitantly with ACE inhibitors and/or angiotensin II receptor antagonists [see Warnings and Precautions (5.4, 5.6)].

7.8 Antiepileptic Drugs

Sporadic cases of seizures have been reported during concomitant use of ketorolac and antiepileptic drugs (phenytoin, carbamazepine).

7.9 Psychoactive Drugs

Hallucinations have been reported when ketorolac was used in patients taking psychoactive drugs (fluoxetine, thiothixene, alprazolam).

7.10 Pentoxifylline

When ketorolac is administered concurrently with pentoxifylline, there is an increased tendency to bleeding. Therefore, concomitant use of SPRIX and Pentoxifylline is contraindicated [see Contraindications (4) and Warnings and Precautions (5.3)].

7.11 Nondepolarizing Muscle Relaxants

In postmarketing experience there have been reports of a possible interaction between ketorolac and nondepolarizing muscle relaxants that resulted in apnea. The concurrent use of ketorolac with muscle relaxants has not been formally studied.

7.12 Selective Serotonin Reuptake Inhibitors (SSRIs)

There is an increased risk of gastrointestinal bleeding when selective serotonin reuptake inhibitors (SSRIs) are combined with NSAIDs. Use caution when SPRIX is administered concomitantly with SSRIs.

7.13 Fluticasone

The rate and extent of absorption of ketorolac from SPRIX administration (31.5 mg dose) were assessed in subjects with allergic rhinitis before and after the administration of a single daily dose of 200 mcg (as 2 x 50 mcg in each nostril) of fluticasone propionate nasal spray for 7 consecutive days. There was no effect on the pharmacokinetic characteristics of SPRIX that can be considered clinically significant [see Clinical Pharmacology (12.4)].

7.14 Oxymetazoline

The rate and extent of absorption of ketorolac from SPRIX administration were assessed in subjects with allergic rhinitis before and 30 min after a single dose (3 sprays in each nostril) of oxymetazoline hydrochloride nasal spray. There was no effect on the pharmacokinetic characteristics of SPRIX that can be considered clinically significant [see Clinical Pharmacology (12.4)].

8 USE IN SPECIFIC POPULATIONS

8.1 Pregnancy

TERATOGENIC EFFECTS

Teratogenic Effects: Pregnancy Category C prior to 30 weeks gestation; Category D starting at 30 weeks gestation.

SPRIX can cause fetal harm when administered to a pregnant woman. Human data demonstrate that use of NSAIDs at or after 30 weeks gestation increases the risk of premature closure of the ductus arteriosus. If SPRIX is used at or after 30 weeks gestation, the patient should be apprised of the potential hazard to a fetus. There are no adequate, well-controlled studies in pregnant women. Prior to 30 weeks gestation, SPRIX should be used during pregnancy only if the potential benefit justifies the potential risk to the fetus.

Reproduction studies have been performed during organogenesis using daily oral doses of ketorolac tromethamine at 3.6 mg/kg (0.6 times the human systemic exposure at the recommended maximum IN dose of 31.5 mg qid, based on area-under-the-plasma-concentration curve [AUC]) in rabbits and at 10 mg/kg (1.7 times the human AUC) in rats. These studies did not reveal evidence of teratogenicity or other adverse developmental outcomes. However, because animal dosing was limited by maternal toxicity, these studies do not adequately assess ketorolac's potential to cause adverse developmental outcomes in humans.

8.2 Labor and Delivery

The effects of SPRIX on labor and delivery in pregnant women are unknown. In rat studies, maternal exposure to NSAIDs, as with other drugs known to inhibit prostaglandin synthesis, increased the incidence of dystocia and delayed parturition, and decreased pup survival.

8.3 Nursing Mothers

Ketorolac is excreted in human milk. Ten nursing mothers received 10 mg of oral ketorolac, four times a day, for two days. In four women, ketorolac was undetectable in milk (assay limit 5 ng/mL). In the remaining six women, ketorolac concentrations in milk ranged from 5.2 to 7.9 ng/mL. Based on these concentrations, the estimated maximum infant daily dose of ketorolac from breast milk is 1.185 mcg/kg/day. Exercise caution when administering SPRIX to a nursing woman.

8.4 Pediatric Use

The safety and effectiveness of ketorolac in pediatric patients 17 years of age and younger have not been established.

8.5 Geriatric Use (≥ 65 years of age)

Exercise caution when treating the elderly (65 years and older) with SPRIX. Carefully consider the potential benefits and risks of SPRIX and other treatment options before deciding to use SPRIX. Use the lowest effective dose for the shortest duration consistent with individual patient treatment goals [see Dosage and Administration (2.3), Warnings and Precautions (5.2), Clinical Pharmacology (12.4)]. After observing the response to initial therapy with SPRIX, then adjust the dose and frequency to suit an individual patient's needs.

9 DRUG ABUSE AND DEPENDENCE

Ketorolac does not bind to opiate receptors. A study to evaluate the sedative and addictive potential of ketorolac in volunteers showed no withdrawal symptoms upon cessation of dosing with ketorolac 30 mg IM 4 times daily for 5 days. A single-dose clinical study of IM ketorolac showed no significant adverse effects on psychomotor measurements, including reaction time, computerized driving skills, ataxia, and sedation.

10 OVERDOSAGE

There has been no experience with overdosage of SPRIX. In controlled overdosage studies with IM ketorolac injection, daily doses of 360 mg given for five days (approximately 3 times the maximum daily dose of SPRIX) caused abdominal pain and peptic ulcers, which healed after discontinuation of dosing. Single overdoses of ketorolac tromethamine have been variously associated with abdominal pain, nausea, vomiting, hyperventilation, peptic ulcers and/or erosive gastritis, and renal dysfunction.

Symptoms and Signs

Symptoms following acute NSAID overdose are usually limited to lethargy, drowsiness, nausea, vomiting, and epigastric pain, which are generally reversible with supportive care. Gastrointestinal bleeding can occur. Hypertension, acute renal failure, respiratory depression, and coma may occur, but are rare.

Treatment

Manage patients using symptomatic and supportive care following an NSAID overdose. There are no specific antidotes. Activated charcoal (60 g to 100 g in adults, 1 g/kg to 2 g/kg in children) may be indicated in patients seen within 4 hours of ingestion with symptoms or following a large oral overdose (5 to 10 times the usual dose). Forced diuresis, alkalization of urine, hemodialysis, or hemoperfusion may not be useful due to high protein binding.

11 DESCRIPTION

Ketorolac tromethamine is a member of the pyrrolo-pyrrole group of nonsteroidal anti-inflammatory drugs (NSAIDs). The chemical name for ketorolac tromethamine is (±)-5-benzoyl-2,3-dihydro-1H-pyrrolizine-1-carboxylic acid, compound with 2-amino-2-(hydroxymethyl)-1,3-propanediol (1:1), and the structural formula is:

The molecular weight of ketorolac tromethamine is 376.41. Ketorolac tromethamine is highly water-soluble, allowing its formulation in an aqueous nasal spray product at pH 7.2.

SPRIX is available as an intranasal spray product containing the active ingredient (ketorolac tromethamine) and the excipients edetate disodium (EDTA), monobasic potassium phosphate, sodium hydroxide, and water for injection.

12 CLINICAL PHARMACOLOGY

12.1 Mechanism of Action

SPRIX contains ketorolac tromethamine, a nonsteroidal anti-inflammatory drug (NSAID). Ketorolac is an analgesic that inhibits the enzyme cyclooxygenase (COX), an early component of the arachidonic acid cascade, resulting in the reduced synthesis of prostaglandins, thromboxanes, and prostacyclin.

Ketorolac does not bind to the opiate receptor subtypes (mu, kappa, delta), but a 30 mg dose of ketorolac tromethamine IM has demonstrated an overall analgesic effect between that obtained with morphine 6 mg and 12 mg. Ketorolac possesses no sedative or anxiolytic properties, and has no effect on gut motility.

12.2 Pharmacodynamics

Ketorolac tromethamine is a racemic mixture of [-]S and [+]R-enantiomeric forms, with the S-form having analgesic activity. Ketorolac, the active component of SPRIX, has anti-inflammatory, analgesic, and anti-pyretic effects. Studies directly comparing the analgesic effects of SPRIX and opioids have not been conducted.

12.3 Pharmacokinetics

The half-lives of ketorolac by the IN and IM routes were similar. The bioavailability of ketorolac by the IN route of administration of a 31.5 mg dose was approximately 60% compared to IM administration. (See Table 2.)

Table 2: Pharmacokinetic Parameters of Ketorolac Tromethamine after Intramuscular (IM) and Intranasal (IN) Administration
Ketorolac Tromethamine | Cmax (SD) ng/mL | tmax (range) hours | AUC 0-∞ (SD) ng•h/mL | T½ (SD) hours
30 mg IM (1.0 mL of a 30 mg/mL solution) | 2382.2 (432.7) | 0.75 (0.25-1.03) | 11152.8 (4260.1) | 4.80 (1.18)
31.5 mg IN (SPRIX) (2 x 100 μL of a 15% w/w solution) | 1805.8 (882.8) | 0.75 (0.50-2.00) | 7477.3 (3654.4) | 5.24 (1.33)
15 mg IM (0.5 mL of a 30 mg/mL solution) | 1163.4 (279.9) | 0.75 (0.25-1.50) | 5196.3 (2076.7) | 5.00 (1.72)
Cmax = maximum plasma concentration; tmax = time of Cmax; AUC0-∞ = complete area under the concentration-time curve; T½ = half-life; SD = standard deviation. All values are means, except tmax, for which medians are reported.

Absorption: In a study in which SPRIX (31.5 mg) was administered to healthy volunteers four times daily for 5 days, the Cmax, tmax, and AUC values following the final dose were comparable to those obtained in the single-dose study. Accumulation of ketorolac has not been studied in special populations, geriatric, pediatric, renal failure or hepatic disease patients.

Distribution: Scintigraphic assessment of drug disposition of ketorolac following SPRIX intranasal dosing demonstrated that most of the ketorolac was deposited in the nasal cavity and pharynx, with less than 20% deposited in the esophagus and stomach, and zero or negligible deposition in the lungs (<0.5%).

The mean apparent volume (Vβ) of ketorolac tromethamine following complete distribution was approximately 13 liters. This parameter was determined from single-dose data. The ketorolac tromethamine racemate has been shown to be highly protein bound (99%). Nevertheless, plasma concentrations as high as 10 mcg/mL will only occupy approximately 5% of the albumin binding sites. Thus, the unbound fraction for each enantiomer will be constant over the therapeutic range. A decrease in serum albumin, however, will result in increased free drug concentrations. Ketorolac tromethamine is excreted in human milk.

Metabolism: Ketorolac tromethamine is largely metabolized in the liver. The metabolic products are hydroxylated and conjugated forms of the parent drug. The products of metabolism, and some unchanged drug, are excreted in the urine.

Excretion: The principal route of elimination of ketorolac and its metabolites is renal. About 92% of a given dose is found in the urine, approximately 40% as metabolites and 60% as unchanged ketorolac. Approximately 6% of a dose is excreted in the feces. A single-dose study with 10 mg ketorolac tromethamine (n=9) demonstrated that the S-enantiomer is cleared approximately two times faster than the R-enantiomer and that the clearance was independent of the route of administration. This means that the ratio of S/R plasma concentrations decreases with time after each dose. There is little or no inversion of the R- to S- form in humans.

The half-life of the ketorolac tromethamine S-enantiomer was approximately 2.5 hours (SD ± 0.4) compared with 5 hours (SD ± 1.7) for the R-enantiomer. In other studies, the half-life for the racemate has been reported to lie within the range of 5 to 6 hours.

12.4 Special Populations

Drug Interactions: A study was conducted in subjects with symptomatic allergic rhinitis to assess the effects of the commonly used nasal spray products oxymetazoline hydrochloride and fluticasone propionate on the pharmacokinetics of SPRIX. Subjects received a single dose of oxymetazoline nasal spray followed by a single dose (31.5 mg) of SPRIX 30 min later. Subjects also received fluticasone nasal spray (200 mcg as 2 x 50 mcg in each nostril) for seven days, with a single dose (31.5 mg) of SPRIX on the 7th day. Administration of these common IN products had no effect of clinical significance on the rate or extent of ketorolac absorption. In addition, comparison of the pharmacokinetics of SPRIX in subjects with allergic rhinitis to data from a previous study in healthy subjects showed no differences that would be of clinical consequence for the efficacy or safety of SPRIX.

Geriatric Patients: A single-dose study was conducted to compare the pharmacokinetics of SPRIX (31.5 mg) in subjects ≥ age 65 to the pharmacokinetics in subjects < age 65. Exposure to ketorolac was increased by 23% for the ≥ 65 population as compared to subjects < 65. Peak concentrations of 2028 and 1840 ng/mL were observed for the elderly and nonelderly adult populations, respectively, at 0.75 h after dosing. In the elderly population a longer terminal half-life was observed as compared to the nonelderly adults (4.5 h vs. 3.3 h, respectively).

Renal Insufficiency: Based on single-dose data only, the mean half-life of ketorolac tromethamine in renally impaired patients is between 6 and 19 hours, and is dependent on the extent of the impairment. There is poor correlation between creatinine clearance and total ketorolac tromethamine clearance in the elderly and populations with renal impairment (r = 0.5).

In patients with renal disease, the AUC∞ of each enantiomer increased by approximately 100% compared with healthy volunteers. The volume of distribution doubles for the S-enantiomer and increases by 1/5th for the R-enantiomer. The increase in volume of distribution of ketorolac tromethamine implies an increase in unbound fraction. The AUC∞-ratio of the ketorolac tromethamine enantiomers in healthy subjects and patients remained similar, indicating there was no selective excretion of either enantiomer in patients compared to healthy subjects.

Hepatic Insufficiency: There was no significant difference in estimates of half-life, AUC∞ and Cmax in 7 patients with liver disease compared to healthy volunteers.

Race: Pharmacokinetic differences due to race have not been identified.

13 NONCLINICAL TOXICOLOGY

13.1 Carcinogenesis, Mutagenesis, and Impairment of Fertility

Carcinogenesis: An 18-month study in mice with oral doses of ketorolac at 2 mg/kg/day (approximately 1.5 times the human systemic exposure at the recommended maximum IN dose of 31.5 mg qid, based on area-under-the-plasma-concentration curve [AUC]), and a 24-month study in rats at 5 mg/kg/day (approximately 0.8 times the human AUC) showed no evidence of tumorigenicity.

Mutagenesis: Ketorolac was not mutagenic in the Ames test, unscheduled DNA synthesis and repair, or in forward mutation assays. Ketorolac did not cause chromosome breakage in the in vivo mouse micronucleus assay. At 1590 μg/mL and at higher concentrations, ketorolac increased the incidence of chromosomal aberrations in Chinese hamster ovarian cells.

Impairment of fertility: Impairment of fertility did not occur in male or female rats at oral doses of 9 mg/kg (approximately 1.5 times the human AUC) and 16 mg/kg (approximately 2.7 times the human AUC) of ketorolac, respectively.

14 CLINICAL STUDIES

14.1 Postoperative Pain

The effect of SPRIX on acute pain was evaluated in two multi-center, randomized, double-blind, placebo-controlled studies.

In a study of adults who had undergone elective abdominal or orthopedic surgery, 300 patients were randomized and treated with SPRIX or placebo administered every 8 hours and morphine administered via patient controlled analgesia on an as needed basis. Efficacy was demonstrated as a statistically significant greater reduction in the summed pain intensity difference over 48 hours in patients who received SPRIX as compared to those receiving placebo. The clinical relevance of this is reflected in the finding that patients treated with SPRIX required 36% less morphine over 48 hours than patients treated with placebo.

In a study of adults who had undergone elective abdominal surgery, 321 patients were randomized and treated with SPRIX or placebo administered every 6 hours and morphine administered via patient controlled analgesia on an as needed basis. Efficacy was demonstrated as a statistically significant greater reduction in the summed pain intensity difference over 48 hours in patients who received SPRIX as compared to those receiving placebo. The clinical relevance of this is reflected in the finding that patients treated with SPRIX required 26% less morphine over 48 hours than patients treated with placebo.

16 HOW SUPPLIED/STORAGE AND HANDLING

16.1 How Supplied

Preservative-free SPRIX Nasal Spray is supplied in boxes containing 5 single-day nasal spray bottles (NDC 0517-8880-05) or 1 single-day nasal spray bottle (NDC 0517-8880-01). Each single-day nasal spray bottle contains a sufficient quantity of solution to deliver 8 sprays for a total of 126 mg of ketorolac tromethamine. Each spray delivers 15.75 mg of ketorolac tromethamine. The delivery system is designed to administer precisely metered doses of 100 μL per spray.

16.2 Storage

Protect from light and freezing. Store unopened SPRIX between 36°F and 46°F (2°C and 8°C). During use, keep containers of SPRIX Nasal Spray at controlled room temperature, between 59°F and 86°F (15°C and 30°C), out of direct sunlight. Bottles of SPRIX should be discarded within 24 hours of priming.

17 PATIENT COUNSELING INFORMATION

Instruct patients to read the NSAID Medication Guide that accompanies each prescription dispensed. Inform patients of the following information before initiating therapy with SPRIX.

Instruct all patients to read and closely follow the FDA-approved SPRIX Patient Instructions to ensure proper administration of SPRIX. When prescribing SPRIX, inform patients or their caregivers of the potential risks of ketorolac treatment, instruct patients to seek medical advice if they develop treatment-related adverse events, advise patients not to give SPRIX to other family members, and advise patients to discard any unused drug.

17.1 Limitations of Use

Instruct patients not to use SPRIX for more than 5 days. Use of SPRIX alone or in combination with any other ketorolac product for more than 5 days increases the risk for serious complications including GI bleeding and renal injury.

17.2 Gastrointestinal Effects

Ketorolac is a potent NSAID and, like other NSAIDs, may cause serious side effects, such as gastrointestinal bleeding, which may result in hospitalization and even fatal outcome. Although serious GI tract ulcerations and bleeding can occur without warning symptoms, instruct patients to be alert for the signs and symptoms of ulcerations and bleeding, and to ask for medical advice when observing any indicative sign or symptom, including epigastric pain, dyspepsia, melena, and hematemesis. Instruct patients of the importance of this follow-up [see Contraindications (4), Warnings and Precautions (5.2)].

17.3 Renal Effects

SPRIX is eliminated by the kidneys. Advise patients to maintain adequate fluid intake and request medical advice if urine output decreases significantly [see Contraindications (4), Warnings and Precautions (5.4)].

17.4 Cardiovascular Effects

Ketorolac, like other NSAIDs, may cause serious CV events, such as MI or stroke, which may result in hospitalization and even death. Although serious CV events can occur without warning symptoms, advise patients to be alert for the signs and symptoms of chest pain, shortness of breath, weakness, slurring of speech, and that they should ask for medical advice when observing any indicative sign or symptoms. Inform patients of the importance of this follow-up [see Warnings and Precautions (5.6)].

17.5 Adverse Skin Reactions

Ketorolac, like other NSAIDs, can cause serious skin side effects such as exfoliative dermatitis, Stevens-Johnson Syndrome (SJS), and toxic epidermal necrolysis (TEN), which may result in hospitalization and even death. Although serious skin reactions may occur without warning, instruct patients to be alert for the signs and symptoms of skin rash and blisters, fever, or other signs of hypersensitivity such as itching, and should ask for medical advice when observing any indicative signs or symptoms. Advise patients to stop the drug immediately if they develop any type of rash, and contact their physicians as soon as possible [see Warnings and Precautions (5.7)].

17.6 Weight Gain and Edema

Instruct patients to promptly report signs or symptoms of unexplained weight gain or edema to their physicians [see Warnings and Precautions (5.4, 5.6)].

17.7 Hepatotoxicity

Inform patients of the warning signs and symptoms of hepatotoxicity (e.g., nausea, fatigue, lethargy, pruritus, jaundice, right upper quadrant tenderness, and "flu-like" symptoms). If these occur, instruct patients to stop therapy and seek immediate medical therapy [see Warnings and Precautions (5.9)].

17.8 Anaphylactoid Reactions

Inform patients of the signs of an anaphylactoid reaction (e.g., difficulty breathing, swelling of the face or throat). If these occur, instruct patients to seek immediate emergency help [see Contraindications (4), Warnings and Precautions (5.5, 5.11)].

17.9 Effects During Pregnancy

Avoid the use of SPRIX at or beyond 30 weeks gestation as ketorolac can cause premature closure of the ductus arteriosus [see, Warnings and Precautions (5.8), Use in Specific Populations (8.1)].

17.10 Single Day Container

Instruct patients not to use any single bottle of SPRIX for more than one day [see Dosage and Administration (2.4)].

17.11 Nasal Discomfort

Advise patients that they may experience transient, mild to moderate nasal irritation or discomfort upon dosing.

Distributed by:

American Regent, Inc.
Shirley, NY 11967

Medication Guide

For

Non-Steroidal Anti-Inflammatory Drugs (NSAIDs)

(See the end of this Medication Guide for a list of prescription NSAID medicines.)

What is the most important information I should know about medicines called Non-Steroidal Anti-Inflammatory Drugs (NSAIDs)?

NSAID medicines may increase the chance of a heart attack or stroke that can lead to death. This chance increases:

- with longer use of NSAID medicines
- in people who have heart disease

NSAID medicines should never be used right before or after a heart surgery called a “coronary artery bypass graft (CABG).”

NSAID medicines can cause ulcers and bleeding in the stomach and intestines at any time during treatment. Ulcers and bleeding:

- can happen without warning symptoms
- may cause death

The chance of a person getting an ulcer or bleeding increases with:

- taking medicines called “corticosteroids” and “anticoagulants”
- longer use
- smoking
- drinking alcohol
- older age
- having poor health

NSAID medicines should only be used:

- exactly as prescribed
- at the lowest dose possible for your treatment
- for the shortest time needed

What are Non-Steroidal Anti-Inflammatory Drugs (NSAIDs)?

NSAID medicines are used to treat pain and redness, swelling, and heat (inflammation) from medical conditions such as:

- different types of arthritis
- menstrual cramps and other types of short-term pain

Who should not take a Non-Steroidal Anti-Inflammatory Drug (NSAID)?

Do not take an NSAID medicine:

- if you had an asthma attack, hives, or other allergic reaction with aspirin or any other NSAID medicine
- for pain right before or after heart bypass surgery

Tell your healthcare provider:

- about all of your medical conditions.
- about all of the medicines you take. NSAIDs and some other medicines can interact with each other and cause serious side effects. Keep a list of your medicines to show to your healthcare provider and pharmacist.
- if you are pregnant. Use of NSAID medicines (at or after 30 weeks of pregnancy) can harm your baby.
- if you are breastfeeding. Some SPRIX® (ketorolac tromethamine) Nasal Spray may pass into your breast milk.

What are the possible side effects of Non-Steroidal Anti-Inflammatory Drugs (NSAIDs)?

Serious side effects include:

- heart attack
- stroke
- high blood pressure
- heart failure from body swelling (fluid retention)
- kidney problems including kidney failure
- bleeding and ulcers in the stomach and intestine
- low red blood cells (anemia)
- life-threatening skin reactions
- life-threatening allergic reactions
- liver problems including liver failure
- asthma attacks in people who have asthma

Other side effects include:

- stomach pain
- constipation
- diarrhea
- gas
- heartburn
- nausea
- vomiting
- dizziness

Get emergency help right away if you have any of the following symptoms:

- shortness of breath or trouble breathing
- chest pain
- weakness in one part or side of your body
- slurred speech
- swelling of the face or throat

Stop your NSAID medicine and call your healthcare provider right away if you have any of the following symptoms:

- nausea
- more tired or weaker than usual
- itching
- your skin or eyes look yellow
- stomach pain
- flu-like symptoms
- vomit blood
- there is blood in your bowel movement or it is black and sticky like tar
- unusual weight gain
- skin rash or blisters with fever
- swelling of the arms and legs, hands and feet

These are not all the side effects with NSAID medicines. Talk to your healthcare provider or pharmacist for more information about NSAID medicines.

Other information about Non-Steroidal Anti-Inflammatory Drugs (NSAIDs):

- Aspirin is an NSAID medicine but it does not increase the chance of a heart attack. Aspirin can cause bleeding in the brain, stomach, and intestines. Aspirin can also cause ulcers in the stomach and intestines.
- Some of these NSAID medicines are sold in lower doses without a prescription (over-the-counter). Talk to your healthcare provider before using over-the-counter NSAIDs for more than 10 days.

NSAID medicines that need a prescription:

Generic Name | Tradename
Celecoxib | Celebrex
Diclofenac | Flector, Cataflam, Voltaren, Arthrotec (combined with misoprostol)
Diflunisal | Dolobid
Etodolac | Lodine, Lodine XL
Fenoprofen | Nalfon, Nalfon 200
Flurbirofen | Ansaid
Ibuprofen | Motrin, Tab-Profen, Vicoprofen (combined with hydrocodone), Combunox (combined with oxycodone)
Indomethacin | Indocin, Indocin SR, Indo-Lemmon, Indomethagan
Ketoprofen | Oruvail
Ketorolac | SPRIX®
Mefenamic Acid | Ponstel
Meloxicam | Mobic
Nabumetone | Relafen
Naproxen | Naprosyn, Anaprox, Anaprox DS, EC-Naproxyn, Naprelan, Naprapac (copackaged with lansoprazole)
Oxaprozin | Daypro
Piroxicam | Feldene
Sulindac | Clinoril
Tolmetin | Tolectin, Tolectin DS, Tolectin 600

This Medication Guide has been approved by the U.S. Food and Drug Administration.

Patient Instructions

Guide to Proper Use of SPRIX® (ketorolac tromethamine) Nasal Spray

Each Nasal Spray Bottle Contains 1 Day's Supply of Pain Medication

Discard each nasal spray bottle within 24 hours of taking your first dose, even if the bottle still contains some unused medication.

Please read this leaflet carefully before you start to take your medicine. It is important that you use SPRIX properly to achieve the desired results.

For further information ask your doctor or pharmacist.

USE OF SPRIX FOR ACUTE MODERATE TO MODERATELY SEVERE PAIN

Your doctor has prescribed SPRIX to treat pain. It is important that you use SPRIX only as prescribed by your doctor. Do not use SPRIX for more than 5 days in a row. If you are still experiencing pain after 5 days, please contact your doctor or healthcare provider.

SPRIX contains ketorolac, a potent non-steroidal anti-inflammatory drug (NSAID) that reduces inflammation and pain. For more information about NSAID products, please see the separate NSAID Medication Guide.

As with all pain medications, it is important that you drink plenty of fluids while you are taking SPRIX.

USING YOUR NASAL SPRAY

Always follow your doctor's instructions about how often to use SPRIX. The doctor will tell you how many sprays you should use each time you take SPRIX. These instructions will provide you with information on how to use the spray bottle.

Some patients experience discomfort or irritation in the nose when using SPRIX. Generally, this lasts only a few minutes and does not worsen when you use SPRIX again. Some people experience a brief sensation in the throat. If this happens, you may want to take a sip of water after using SPRIX.

Components of SPRIX Bottle

FOLLOW THESE SIMPLE INSTRUCTIONS

1. First hold the finger flange with your fingers (See Figure 1), and remove the clear plastic cover with your opposite hand; then remove the blue plastic safety clip. Keep the clear plastic cover; you may throw away the blue plastic safety clip.
  Figure 1
2. Before using the bottle for the FIRST time, you must activate the pump. To activate the pump, hold the bottle at arm's length away from you with your index finger and middle finger resting on the top of the finger flange and your thumb supporting the base (see Figure 2).
  Press down evenly and release the pump 5 times. Note: you may not see a spray the first few times you press down.
  The bottle is now ready to use. There is no need to activate the pump again if you use more doses from this bottle.
  Figure 2
3. It's important to get the medication to the correct place in your nose so it will be most effective. Here's the simple way to do this.
  Blow your nose gently to clear your nostrils.
  Sit up straight or stand. Tilt your head slightly forward.
  Insert the tip of the container into your right nostril.
  Point the container away from the center of your nose (see Figure 3).
  Figure 3
  Spray once into your right nostril, pressing down evenly on both sides, as shown in Figure 3.
  If your doctor has prescribed only one spray per dose for you, you have now completed administration; skip to Step 5 below.
4. If your doctor has prescribed a dose of 2 sprays for you, repeat the process for your left nostril. Again, be sure to point the spray away from the center of your nose. Spray once into your left nostril.
5. Replace the clear plastic cover and place the bottle in a cool, dry location out of direct sunlight, such as inside a medication cabinet. Keep out of reach of children.

DOSING AND ADMINISTRATION

-For adults under 65 years of age, the usual recommended dose is one dose every 6-8 hours, as needed for relief of pain. One dose consists of one spray into each nostril (two sprays in total).-For adults 65 years of age or older, the usual recommended dose is one dose every 6-8 hours, as needed. One dose consists of one spray into either nostril (one spray in total).-Do not use more than the prescribed amount, and do not use more frequently than once every 6 hours.

STORING AND DISCARDING YOUR CONTAINERS

-Keep SPRIX upright in a cool, dry location out of direct sunlight.-SPRIX does not contain a preservative. It is important that you throw away each bottle of SPRIX within 24 hours of administering the first dose. Once a bottle has been used, do not keep it for more than 24 hours.-Always keep SPRIX out of the reach of children.-Do not allow SPRIX to become frozen.-Discard in the trash (non-recyclable).

ASSEMBLY INSTRUCTIONS

-If the clear plastic cover is improperly removed, the top portion of the nasal spray may be pulled off of the glass vial. If this happens, reinsert the top portion back onto the glass vial by lining it up carefully and softly pushing it back on until it is back in the correct position (See Figure 4). The nasal spray bottle will now work properly again.

Figure 4

FOR MORE INFORMATION

If you have any questions about SPRIX, or are unsure about something, you should ask your doctor or pharmacist.

Do not throw this leaflet away, so you may read it again when you administer additional doses or begin using a new bottle of SPRIX Nasal Spray.

Distributed by:

American Regent, Inc.
Shirley, NY 11967

Rev. 1/11

Repacked by:

H.J. Harkins Company, Inc.

Grover Beach, CA 93433

Principal Display Panel – Bottle Label

SPRIX®

(ketorolac tromethamine)

Nasal Spray

15.75 mg per spray

Rx Only